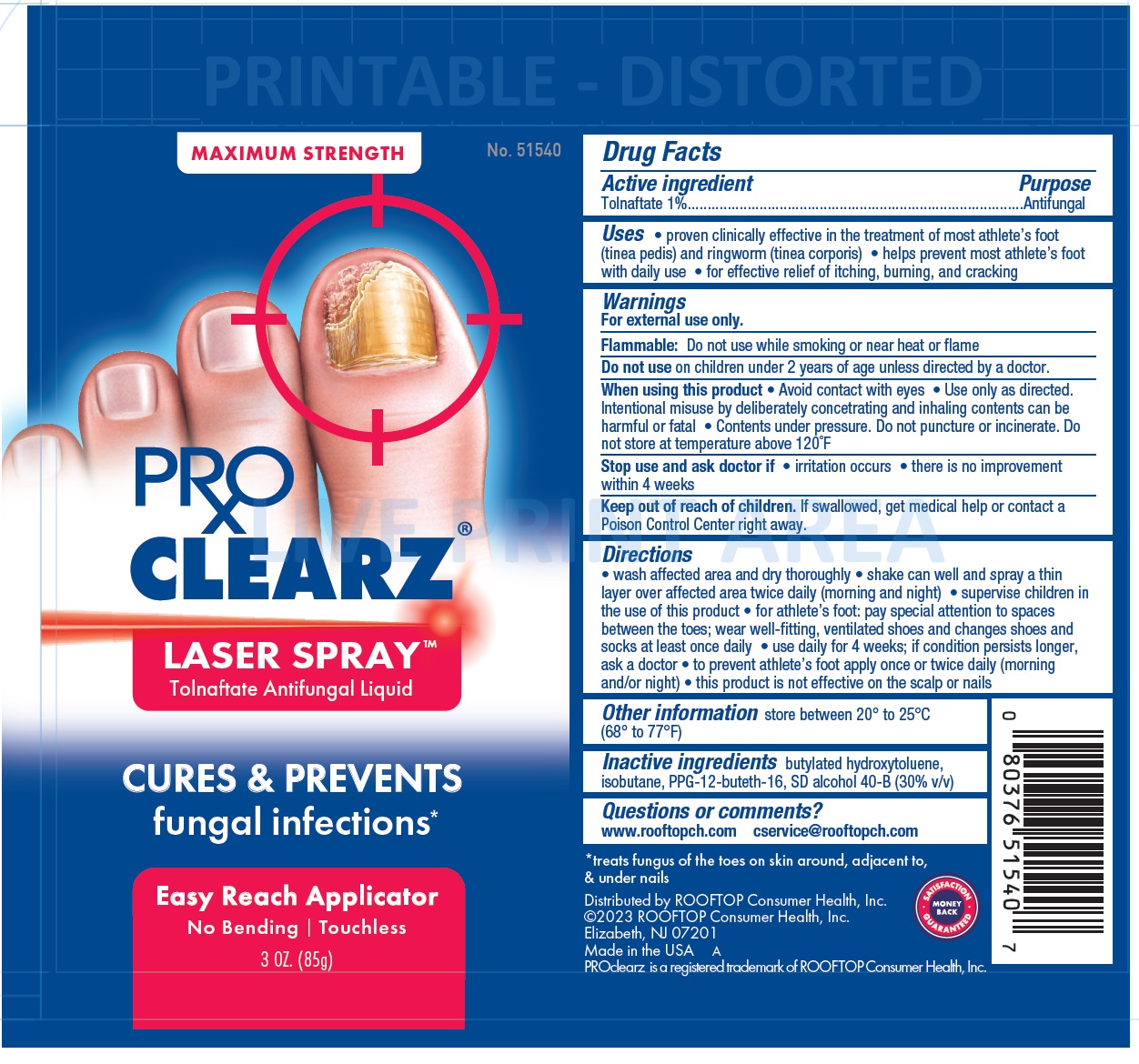 DRUG LABEL: ProClearz Laser Antifungal
NDC: 29784-183 | Form: LIQUID
Manufacturer: Rooftop Consumer Health, inc
Category: otc | Type: HUMAN OTC DRUG LABEL
Date: 20260129

ACTIVE INGREDIENTS: TOLNAFTATE 10 mg/1 g
INACTIVE INGREDIENTS: BUTYLATED HYDROXYTOLUENE; ISOBUTANE; PPG-12-BUTETH-16; ALCOHOL

ProClearz Laser Spray Antifungal

Active ingredient

Tolnaftate 1%

Purpose

Antifungal

Uses

- proven clinically effective in the treatment of most athlete’s foot (tinea pedis) and ringworm (tinea corporis)
- helps prevent most athlete’s foot with daily use
- for effective relief of itching, burning, and cracking

Warnings

For external use only.

Flammable:Do not use while smoking or near heat or flame

Do not use

on children under 2 years of age unless directed by a doctor.

When using this product

- Avoid contact with eyes
- Use only as directed. Intentional misuse by deliberately concetrating and inhaling contents can be harmful or fatal
- Contents under pressure. Do not puncture or incinerate. Do not store at temperature above 120°F

Stop use and ask doctor if

- irritation occurs
- there is no improvement within 4 weeks

Keep out of reach of children.

If swallowed, get medical help or contact a Poison Control Center right away.

Directions

- wash affected area and dry thoroughly
- shake can well and spray a thin layer over affected area twice daily (morning and night)
- supervise children in the use of this product
- for athlete’s foot: pay special attention to spaces between the toes; wear well-fitting, ventilated shoes and changes shoes and socks at least once daily
- use daily for 4 weeks; if condition persists longer, ask a doctor
- to prevent athlete’s foot apply once or twice daily (morning and/or night)
- this product is not effective on the scalp or nails

Other information

store between 20° to 25°C (68° to 77°F)

Inactive ingredients

butylated hydroxytoluene, isobutane, PPG-12-buteth-16, SD alcohol 40-B (30% v/v)

Questions or comments?

www.rooftopch.com cservice@rooftopch.com